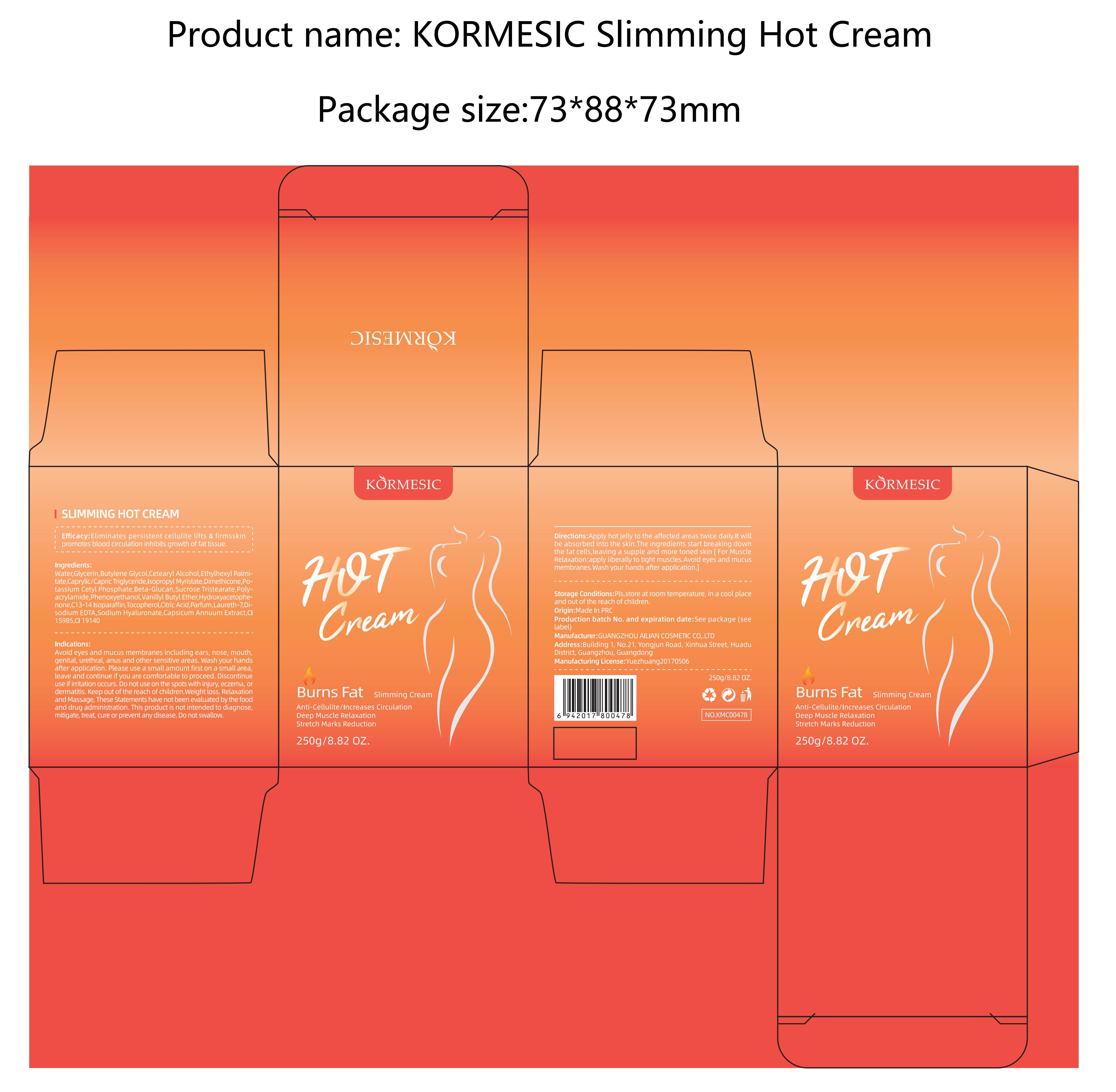 DRUG LABEL: Kormesic slimming hot cream
NDC: 84613-011 | Form: CREAM
Manufacturer: Shenzhen Xingqi Technology Co., Ltd.
Category: otc | Type: HUMAN OTC DRUG LABEL
Date: 20240804

ACTIVE INGREDIENTS: TOCOPHEROL 1 g/100 g
INACTIVE INGREDIENTS: SUCROSE TRISTEARATE; POLYACRYLAMIDE (1500 MW); CETOSTEARYL ALCOHOL; CAPSICUM; PHENOXYETHANOL; VANILLYL BUTYL ETHER; HYDROXYACETOPHENONE; CITRIC ACID MONOHYDRATE; ETHYLHEXYL PALMITATE; YEAST .BETA.-D-GLUCAN; GLYCERIN; ISOPROPYL MYRISTATE; LAURETH-7; FD&C YELLOW NO. 5; WATER; BUTYLENE GLYCOL; DIMETHICONE; C13-14 ISOPARAFFIN; MEDIUM-CHAIN TRIGLYCERIDES; POTASSIUM CETYL PHOSPHATE; PARFUMIDINE; EDETATE DISODIUM; HYALURONATE SODIUM; FD&C YELLOW NO. 6

Active ingredients

Tocopherol 1%

Purpose

Eliminates persistent cellulite lifts & firmsskin promotes blood circulation inhibits growth of fat tissue.

uses

Apply hot jelly to the affected areas twice daily.It will be absorbed into the skin.The ingredients start breaking down the fat cells,leaving a supple and more toned skin [ For Muscle Relaxation:apply liberally to tight muscles.Avoid eyes and mucus membranes.Wash your hands after application.]

WARNINGS

Avoid eyes and mucus membranes including ears, nose, mouth, genital, urethral, anus and other sensitive areas. Wash your hands after application. Please use a small amount first on a small area, leave and continue if you are comfortable to proceed.Discontinue use if irritation occurs. Do not use on the spots with injury, eczema, or dermatitis. Keep out of the reach of children.Weight loss, Relaxation and Massage,These Statements have not been evaluated by the food and drug administration. This product is not intended to diagnose,mitigate, treat, cure or prevent any disease. Do not swallow.

Dosage and administration

For external use only.

Do not use

Avoid eyes and mucus membranes including ears, nose, mouth, genital, urethral, anus and other sensitive areas. Wash your hands after application. Please use a small amount first on a small area, leave and continue if you are comfortable to proceed.Discontinue use if irritation occurs. Do not use on the spots with injury, eczema, or dermatitis. Keep out of the reach of children.Weight loss, Relaxation and Massage, These Statements have not been evaluated by the food and drug administration. This product is not intended to diagnose, mitigate, treat, cure or prevent any disease. Do not swallow.

When using section

When using this product, avoid contact with eyes. lf contact occurs, rinse thoroughly with waterDiscontinue use if any irritation or adverse reaction occurs.

Keep out of reach of children.

Keep out of the reach of children.

Inactive ingredients

Water,Butylene Glycol,Cetearyl Alcohol,Ethylhexyl Palmitate,Caprylic/Capric Triglyceride,Isopropyl Myristate,Dimethicone,Potassium Cetyl Phosphate,Beta-Glucan,Sucrose Tristearate,Polyacrylamide,Phenoxyethanol,Vanillyl Butyl Ether,Hydroxyacetophenone,C13-14 Isoparaffin,Citric Acid,Parfum,Laureth-7,Disodium EDTA,Sodium Hyaluronate,Capsicum Annuum Extract,Cl 15985,CI 19140